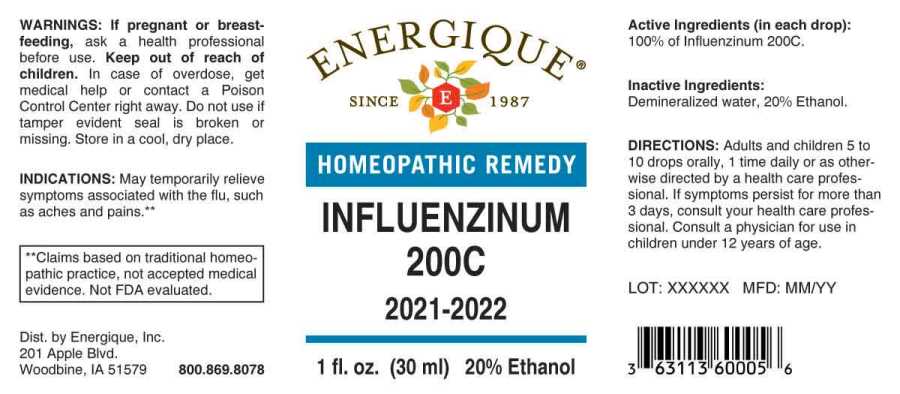 DRUG LABEL: Influenzinum 200C
NDC: 44911-0652 | Form: LIQUID
Manufacturer: Energique, Inc.
Category: homeopathic | Type: HUMAN OTC DRUG LABEL
Date: 20221229

ACTIVE INGREDIENTS: INFLUENZA A VIRUS A/VICTORIA/2570/2019 IVR-215 (H1N1) ANTIGEN (FORMALDEHYDE INACTIVATED) 200 [hp_C]/1 mL; INFLUENZA A VIRUS A/TASMANIA/503/2020 IVR-221 (H3N2) ANTIGEN (FORMALDEHYDE INACTIVATED) 200 [hp_C]/1 mL; INFLUENZA B VIRUS B/WASHINGTON/02/2019 ANTIGEN (FORMALDEHYDE INACTIVATED) 200 [hp_C]/1 mL; INFLUENZA B VIRUS B/PHUKET/3073/2013 ANTIGEN (FORMALDEHYDE INACTIVATED) 200 [hp_C]/1 mL
INACTIVE INGREDIENTS: WATER; ALCOHOL

Drug Facts:

ACTIVE INGREDIENT:

(in each drop): 100% of Influenzinum 200C.

INDICATIONS:

May temporarily relieve symptoms associated with the flu, such as aches and pains.**

**Claims based on traditional homeopathic practice, not accepted medical evidence. Not FDA evaluated.

WARNINGS:

If pregnant or breastfeeding, ask a health professional before use.

Keep out of reach of children. In case of overdose, get medical help or contact a Poison Control Center right away.

Do not use if tamper evident seal is broken or missing.

Store in a cool, dry place.

Keep out of reach of children. In case of overdose, get medical help or contact a Poison Control Center right away.

DIRECTIONS:

Adults and children 5 to 10 drops orally, 1 time daily or as otherwise directed by a health care professional. If symptoms persist for more than 3 days, consult your health care professional. Consult a physician for use in children under 12 years of age.

INDICATIONS:

May temporarily relieve symptoms associated with the flu, such as aches and pains.**

**Claims based on traditional homeopathic practice, not accepted medical evidence. Not FDA evaluated.

INACTIVE INGREDIENTS:

Demineralized water, 20% Ethanol

QUESTIONS:

Dist. by Energique, Inc.
201 Apple Blvd.
Woodbine, IA 51579 800.869.8078

PACKAGE LABEL DISPLAY:

ENERGIQUE

SINCE 1987

HOMEOPATHIC REMEDY

INFLUENZINUM
200C
2021-2022

1 fl. oz. (30 ml)